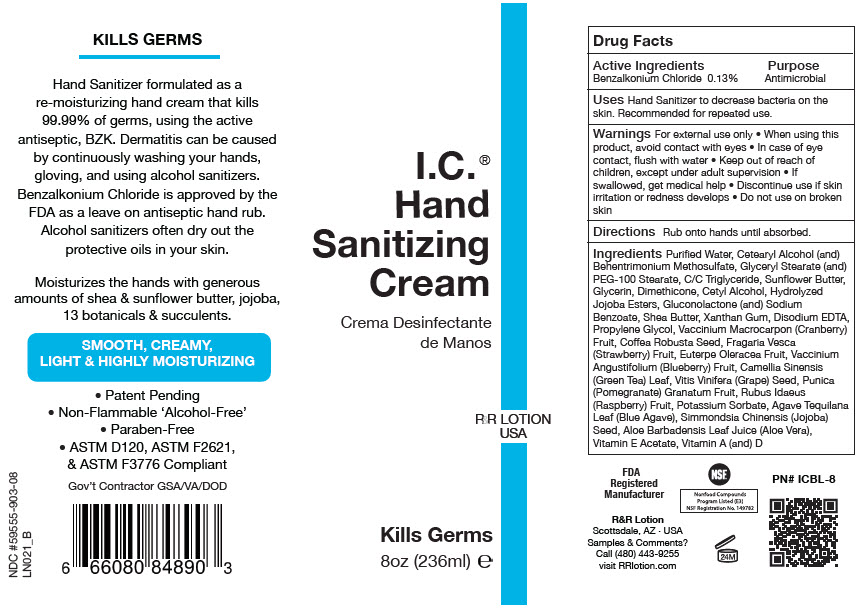 DRUG LABEL: I.C. Sanitizer and Re-Moisturizer with Benzalkonium Chloride
NDC: 59555-903 | Form: LOTION
Manufacturer: R & R Lotion, Inc
Category: otc | Type: HUMAN OTC DRUG LABEL
Date: 20250910

ACTIVE INGREDIENTS: Benzalkonium Chloride 1.3 mg/1 mL
INACTIVE INGREDIENTS: Water; Cetostearyl Alcohol; Behentrimonium Methosulfate; Glyceryl Monostearate; PEG-100 Stearate; Medium-Chain Triglycerides; HELIANTHUS ANNUUS SEED WAX; Glycerin; Dimethicone; Cetyl Alcohol; POTASSIUM HYDROLYZED JOJOBA ESTERS; Gluconolactone; Sodium Benzoate; Shea Butter; Paraffin; Xanthan Gum; EDETATE DISODIUM; PROPYLENE GLYCOL; CRANBERRY; ROBUSTA COFFEE BEAN; FRAGARIA VESCA FRUIT; ACAI; LOWBUSH BLUEBERRY; GREEN TEA LEAF; VITIS VINIFERA SEED PROANTHOCYANIDINS; POMEGRANATE; RASPBERRY; POTASSIUM SORBATE; AGAVE TEQUILANA LEAF; SIMMONDSIA CHINENSIS SEED; ALOE VERA LEAF JUICE; .Alpha.-Tocopherol Acetate; Vitamin A Palmitate; Cholecalciferol

I.C.® Sanitizer and Re-Moisturizer with Benzalkonium Chloride

Drug Facts

Active Ingredients

Benzalkonium Chloride 0.13%

Purpose

Antimicrobial

Uses

Hand Sanitizer to decrease bacteria on the skin. Recommended for repeated use.

Warnings

For external use only

- When using this product, avoid contact with eyes
- In case of eye contact, flush with water

- Keep out of reach of children, except under adult supervision
- If swallowed, get medical help
- Discontinue use if skin irritation or redness develops
- Do not use on broken skin

Directions

Rub onto hands until absorbed.

Ingredients

Purified Water, Cetearyl Alcohol (and) Behentrimonium Methosulfate, Glyceryl Stearate (and) PEG-100 Stearate, C/C Triglyceride, Sunflower Butter, Glycerin, Dimethicone, Cetyl Alcohol, Hydrolyzed Jojoba Esters, Gluconolactone (and) Sodium Benzoate, Shea Butter, Xanthan Gum, Disodium EDTA, Propylene Glycol, Vaccinium Macrocarpon (Cranberry) Fruit, Coffea Robusta Seed, Fragaria Vesca (Strawberry) Fruit, Euterpe Oleracea Fruit, Vaccinium Angustifolium (Blueberry) Fruit, Camellia Sinensis (Green Tea) Leaf, Vitis Vinifera (Grape) Seed, Punica (Pomegranate) Granatum Fruit, Rubus Idaeus (Raspberry) Fruit, Potassium Sorbate, Agave Tequilana Leaf (Blue Agave), Simmondsia Chinensis (Jojoba) Seed, Aloe Barbadensis Leaf Juice (Aloe Vera), Vitamin E Acetate, Vitamin A (and) D

Samples & Comments?

Call (480) 443-9255
visit RRlotion.com

PRINCIPAL DISPLAY PANEL - 236 mL Bottle Label

I.C.®
Hand
Sanitizing
Cream

R&R LOTION
USA

Kills Germs

8oz (236ml) ℮